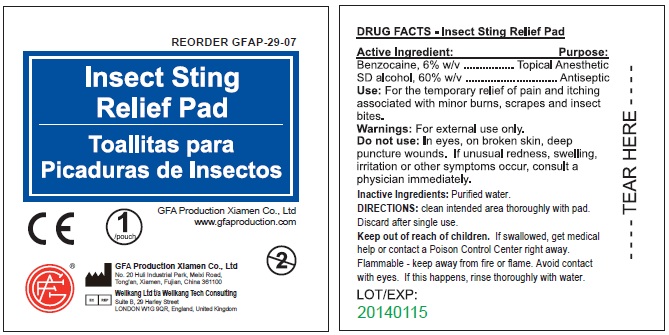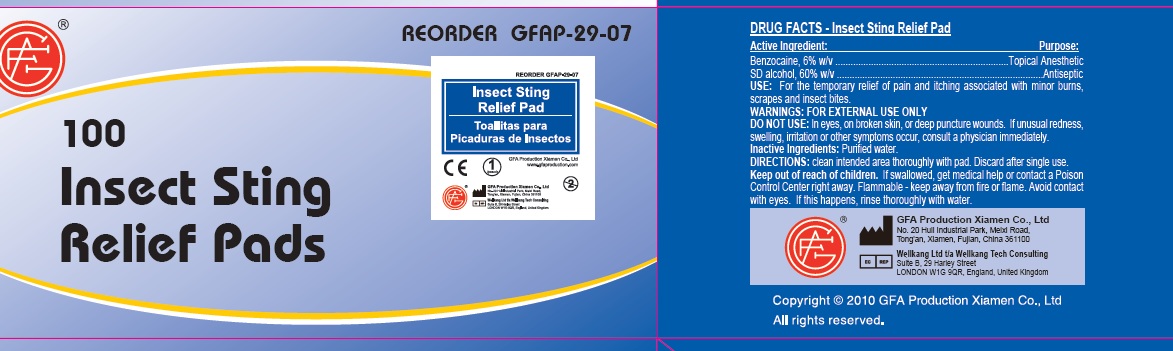 DRUG LABEL: Insect Sting Relief Pad
                        
NDC: 52124-0008 | Form: SWAB
Manufacturer: Genuine First Aid LLC
Category: otc | Type: HUMAN OTC DRUG LABEL
Date: 20111128

ACTIVE INGREDIENTS: BENZOCAINE 6 mL/100 mL; ALCOHOL 60 mL/100 mL
INACTIVE INGREDIENTS: WATER

Insect Sting Relief Pad

Active Ingredient

Active Ingredient: Purpose:

Benzocaine, 6% w/v

SD alcohol, 60% w/v

Purpose

Topical Anesthetic
Antiseptic

Uses

Use: For the temporary relief of pain and itching associated with minor burns, scrapes and insect bites.

Directions

Clean intended area thoroughly with pad. Discard after single use.

Warnings

Warnings: For external use only.

Avoid contact with eyes. If this happens, rinse thoroughly with water.

Keep out of reach of children

If swallowed, get medical help or contact a Poison Control Center right away.

Inactive Ingredients

Purified water

STORAGE AND HANDLING

Flammable - keep away from fire or flame.

Do not use: In eyes, on broken skin, deep puncture wounds. If unusual redness, swelling, irritation or other symptoms occur, consult a physician immediately.

DESCRIPTION

Made in CHINA

LOT/EXP:

PACKAGE LABEL

Insect Sting Relief Pad

Genuine First Aid LLC, Clearwater FL 33755
www.GenuineFirstAid.com
1/pouch
GENUINE FIRST AID